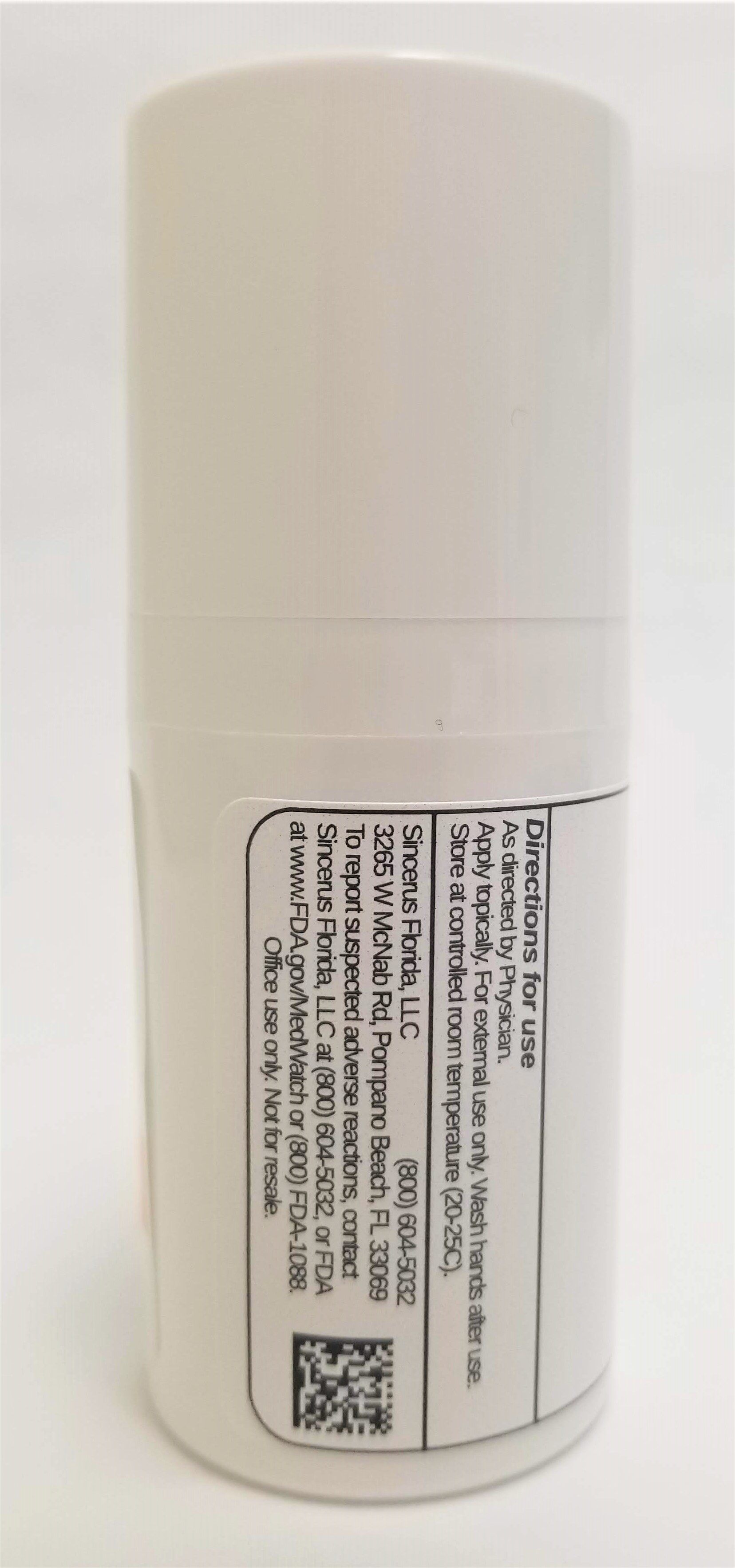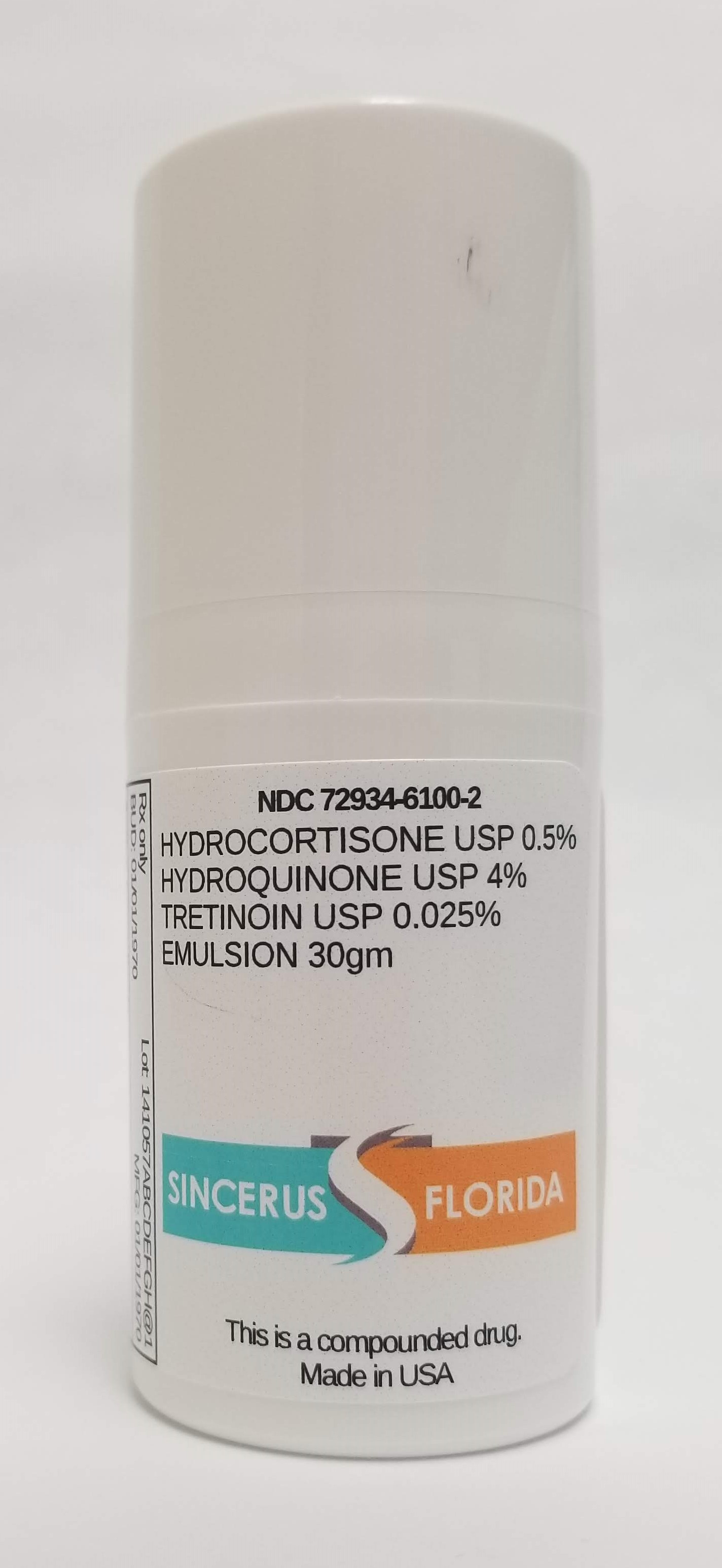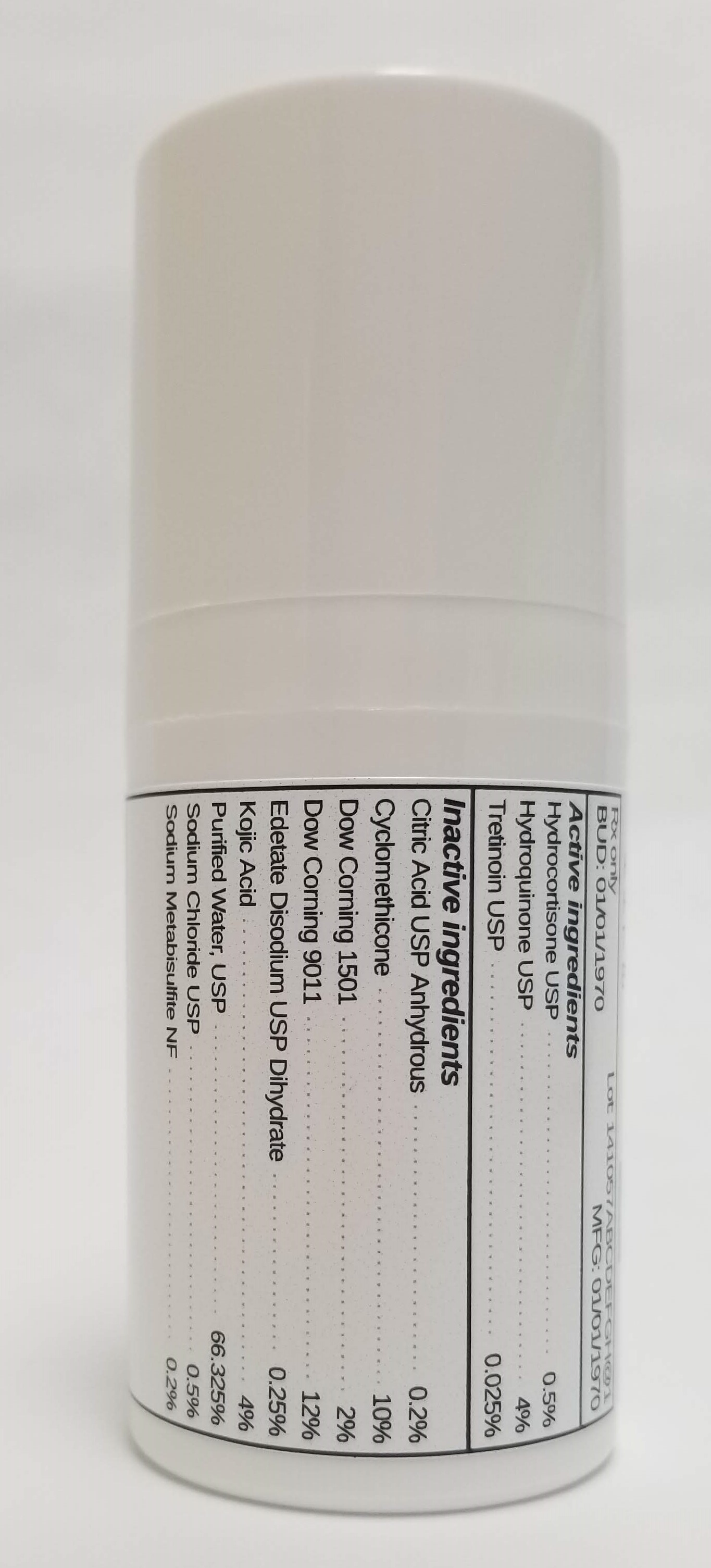 DRUG LABEL: HYDROCORTISONE 0.5% / HYDROQUINONE 4% / TRETINOIN 0.025%
NDC: 72934-6100 | Form: EMULSION
Manufacturer: Sincerus Florda, LLC
Category: prescription | Type: HUMAN PRESCRIPTION DRUG LABEL
Date: 20190517

ACTIVE INGREDIENTS: HYDROCORTISONE 0.5 g/100 g; HYDROQUINONE 4 g/100 g; TRETINOIN 0.025 g/100 g

HYDROCORTISONE 0.5% / HYDROQUINONE 4% / TRETINOIN 0.025%